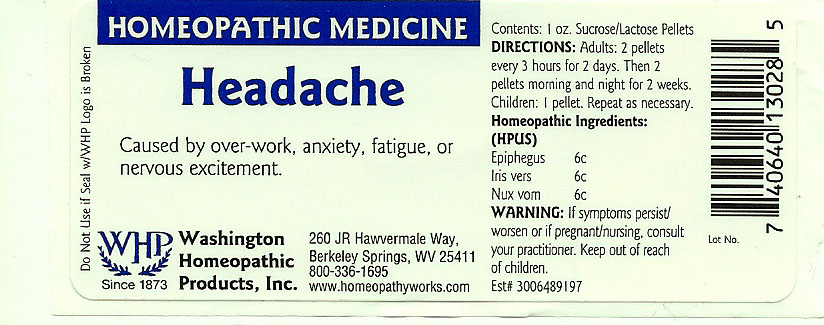 DRUG LABEL: Headache
NDC: 68428-023 | Form: PELLET
Manufacturer: Washington Homeopathic Products
Category: homeopathic | Type: HUMAN OTC DRUG LABEL
Date: 20191223

ACTIVE INGREDIENTS: EPIFAGUS VIRGINIANA 6 [hp_C]/1 1; IRIS VERSICOLOR ROOT 6 [hp_C]/1 1; STRYCHNOS NUX-VOMICA SEED 6 [hp_C]/1 1
INACTIVE INGREDIENTS: SUCROSE; LACTOSE

DRUG FACTS

ACTIVE INGREDIENTS

EPIPHEGUS 6C

IRIS VERS 6C

NUX VOM 6C

USES

To relieve the symptoms caused by over-work, anxiety, fatigue, or nervous excitement.

KEEP OUT OF REACH OF CHILDREN

Keep this and all medicines out of reach of children.

INDICATIONS

EPIPHEGUS Headache

IRIS VERS Headache

NUX VOM Vomiting

STOP USE AND ASK DOCTOR

If symptoms persist/worsen or if pregnant/nursing, stop use and consult your practitioner.

DIRECTIONS

Adults 2 pellets every 3 hours for 2 days. Then 2 pellets morning and night for 2 weeks.

Children: 1 pellet. Repeat as necessary.

INACTIVE INGREDIENTS

Sucrose/Lactose

PRINCIPAL DISPLAY PANEL

Enter section text here